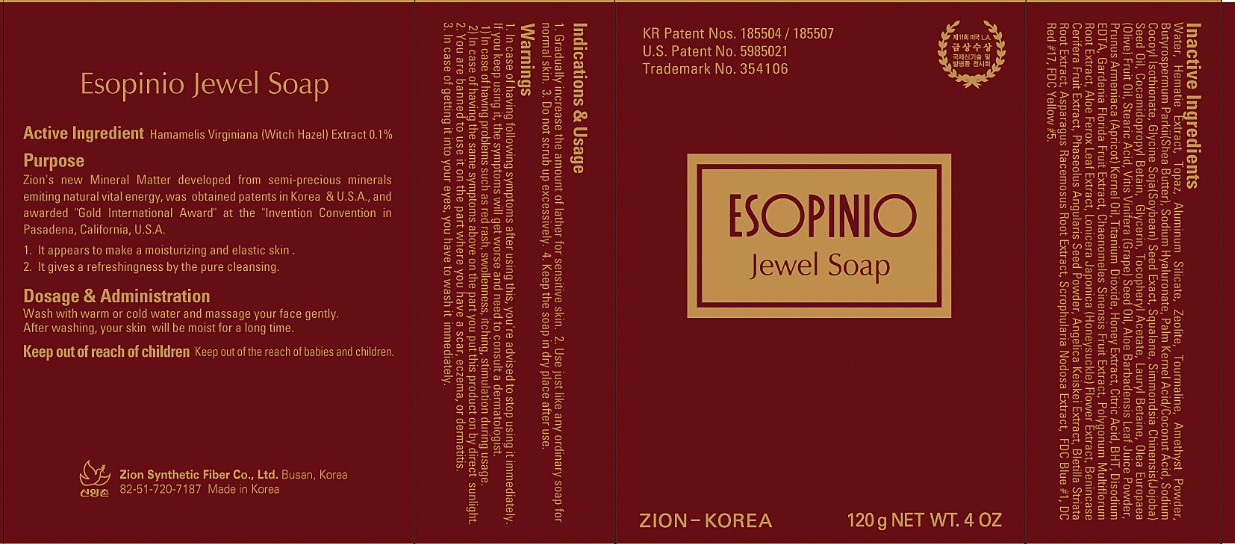 DRUG LABEL: ESOPINIO JEWEL
NDC: 44781-200 | Form: SOAP
Manufacturer: ZION SYNTHETIC FIBER CO., LTD.
Category: otc | Type: HUMAN OTC DRUG LABEL
Date: 20110918

ACTIVE INGREDIENTS: WITCH HAZEL 0.12 g/120 g
INACTIVE INGREDIENTS: Water; ALUMINUM SILICATE; SHEA BUTTER; HYALURONATE SODIUM; COCONUT; PALM KERNEL OIL; SQUALANE; COCAMIDOPROPYL BETAINE; GLYCERIN; OLIVE OIL; STEARIC ACID; WINE GRAPE; ALOE VERA LEAF; APRICOT; TITANIUM DIOXIDE; HONEY; CITRIC ACID MONOHYDRATE; BUTYLATED HYDROXYTOLUENE; EDETATE DISODIUM; ALOE FEROX LEAF; SCROPHULARIA NODOSA

Drug Facts

Active ingredient: WITCH HAZEL 0.1%

Inactive ingredients:
Water, Hematie Extract, Topaz, Aluminum Silicate, Zeolite, Tourmaline, Amethyst Powder, Butyrospermum Parkii(Shea Butter), Sodium Hyaluronate, Palm Kernel Acid/Coconut Acid, Sodium Cocoyl Isothionate, Glycine Soja(Soybean) Seed Exact, Squalane, Simmondsia Chinensis(Jojoba) Seed Oil, Cocamidopropyl Betain, Glycerin, Tocopheryl Acetate, Lauryl Betaine, Olea Europaea (Olive) Fruit Oil,
Stearic Acid, Vitis Vinifera (Grape) Seed Oil, Aloe Barbadensis Leaf Juice Powder, Prunus Armeniaca (Apricot) Kernel Oil, Titanium Dioxide, Honey Extract, Citric Acid, BHT, Disodium EDTA, Gardenia Florida Fruit Extract, Chaenomeles Sinensis Fruit Extract, Polygonum Multiflorum Root Extract, Aloe Ferox Leaf Extract, Lonicera Japonica (Honeysuckle) Flower Extract, Benincase Cerifera Fruit Extract, Phaseolus Angularis Seed Powder, Angelica Keiskei Extract, Bletilla Striata Root Extract, Asparagus Racemosus Root Extract, Scrophularia Nodosa Extract

Purpose:
It appears to make a moisturizing and elastic skin.
It gives a refreshingness by the pure cleansing.

Warnings:
In case of having following symptoms after using this, you're advised to stop using it immediately. If you keep using it, the symptoms will get worse and need to consult a dermatologist.
- In case of having problems such as red rash, swollenness, itching, stimulation during usage.
- In case of having the same symptoms above on the part you put this product on by direct sunlight.
You are banned to use it on the part where you have a scar, eczema, or dermatitis.
In case of getting it into your eyes, you have to wash it immediately.

Keep out of reach of children:
Keep out of the reach of babies and children.

Indication and usage:
Gradually increase the amount of lather for sensitive skin.
Use just like any ordinary soap for normal skin.
Do not scrub up excessively.
Keep the soap in dry place after use.

Dosage and administration:
Wash with warm or cold water and massage your face gently.
After washing, your skin will be moist for a long time.